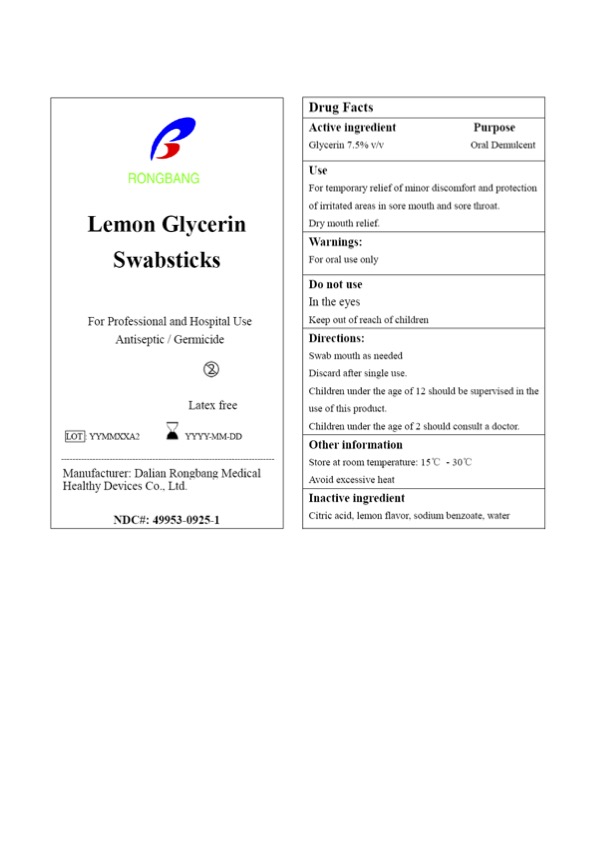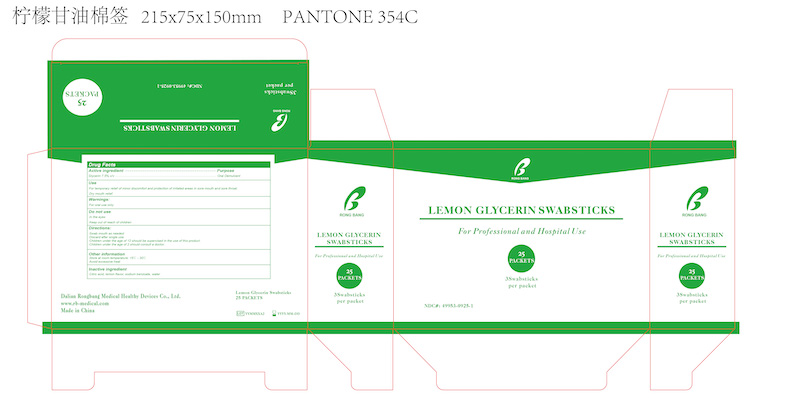 DRUG LABEL: Lemon Glycerin Swabsticks
NDC: 49953-0925 | Form: SWAB
Manufacturer: Dalian Rongbang Medical Healthy Devices Co., Ltd.
Category: otc | Type: HUMAN OTC DRUG LABEL
Date: 20231228

ACTIVE INGREDIENTS: GLYCERIN 7.5 g/100 g
INACTIVE INGREDIENTS: WATER; CITRIC ACID MONOHYDRATE; SODIUM BENZOATE

Dalian Rongbang Lemon Glycerin Swabsticks

ACTIVE INGREDIENT

Glycerin 7.5% v/v

PURPOSE

Oral Demulcent

USE

For temporary relief of minor discomfort and protection of irritated areas in sore mouth and sore throat.

Dry mouth relief.

WARNINGS

For oral use only

DO NOT USE

In the eyes

Keep out of reach of children

Directions

Swab mouth as needed

Discard after single use.

Children under the age of 12 should be supervised in the use of this product.

Children under the age of 2 should consult a doctor.

Other information

Store at room temperature: 15°C - 30°C

Avoid excessive heat

INACTIVE INGREDIENT

Citric acid, lemon flavor, sodium benzoate, water